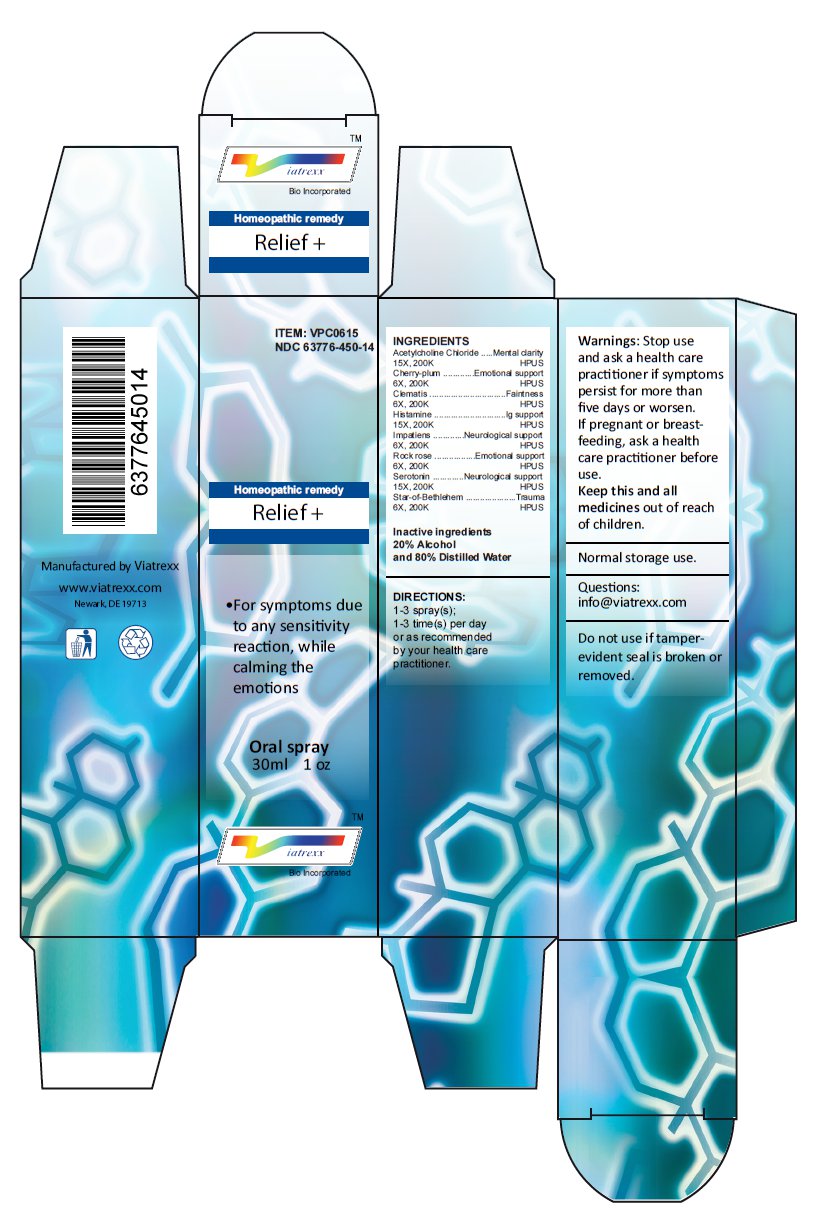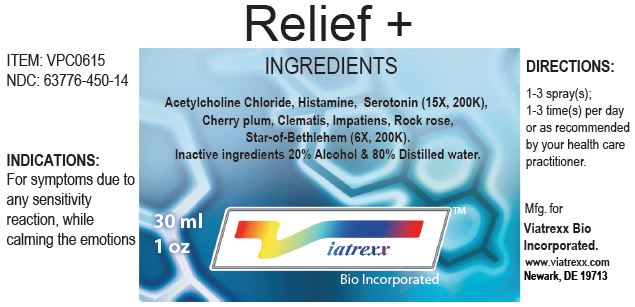 DRUG LABEL: Relief 

NDC: 63776-450 | Form: SPRAY
Manufacturer: VIATREXX BIO INCORPORATED
Category: homeopathic | Type: HUMAN OTC DRUG LABEL
Date: 20221130

ACTIVE INGREDIENTS: HELIANTHEMUM NUMMULARIUM FLOWER 200 [kp_C]/1 mL; SEROTONIN 200 [kp_C]/1 mL; ORNITHOGALUM UMBELLATUM 200 [kp_C]/1 mL; ACETYLCHOLINE CHLORIDE 200 [kp_C]/1 mL; PRUNUS CERASIFERA FLOWER 200 [kp_C]/1 mL; CLEMATIS VITALBA FLOWER 200 [kp_C]/1 mL; HISTAMINE 200 [kp_C]/1 mL; IMPATIENS GLANDULIFERA FLOWER 200 [kp_C]/1 mL
INACTIVE INGREDIENTS: ALCOHOL; WATER

Relief +

Active Ingredients

Acetylcholine Chloride 15X 200K, Cherry-plum 6X 200K, Clematis 6X 200K, Histamine 15X 200K, Impatiens 6X 200K, Rock rose 6X 200K, Serotonin 15X 200K, Star-of-Bethlehem 6X 200K

Purpose:

Acetylcholine Chloride | Mental clarity
Cherry-plum | Emotional support
Clematis | Faintness
Histamine | Ig support
Impatiens | Neurological support
Rock rose | Emotional support
Serotonin | Neurological support
Star-of-Bethlehem | Trauma

Uses

For symptoms due to any sensitivity reaction, while calming the emotions

Warnings

Stop use and ask a health care practitioner if symptoms persist for more than five days or worsen. If pregnant or breastfeeding, ask a health care practitioner before use.

Dosage

1-3 spray(s); 1-3 time(s) per day or as recommended by your health care practitioner.

KEEP OUT OF REACH OF CHILDREN

Keep this and all medicines out of reach of children.

Other Ingredients

Alcohol and Water

Other Information

Normal storage use.
Do not use if tamper-evident seal is broken or removed.

Questions

info@viatrexx.com

Principal Display Panel

ITEM: VPC0615
NDC 63776-450-14
Homeopathic remedy
Relief +
• For symptoms due to any sensitivity reaction, while calming the emotions
Oral spray
30ml 1 oz
Viatrexx™ Bio Incorporated
Manufactured by Viatrexx
www.viatrexx.com
Newark, DE 19713

Relief +
30 mL
1 oz
Viatrexx™ Bio Incorporated
ITEM: VPC0615
NDC: 63776-450-14
INDICATIONS:
For symptoms due to any sensitivity reaction, while calming the emotions
DIRECTIONS:
1-3 spray(s); 1-3 time(s) per day or as recommended by your health care practitioner.
Mfg. for
Viatrexx Bio Incorporated.
www.viatrexx.com
Newark, DE 19713